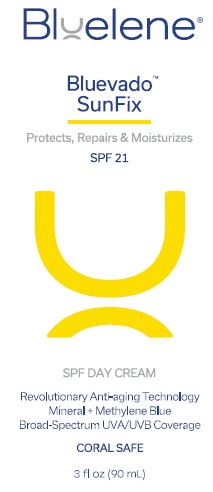 DRUG LABEL: Bluevado Sunfix
NDC: 77358-201 | Form: LOTION
Manufacturer: Magic Blue, LLC
Category: otc | Type: HUMAN OTC DRUG LABEL
Date: 20260113

ACTIVE INGREDIENTS: ZINC OXIDE 8.2 g/100 mL; TITANIUM DIOXIDE 2.8 g/100 mL
INACTIVE INGREDIENTS: ARGAN OIL; ASCORBYL PALMITATE; LEVOMENOL; SHEA BUTTER; C13-15 ALKANE; MEDIUM-CHAIN TRIGLYCERIDES; CETOSTEARYL ALCOHOL; CETYL ALCOHOL; BERGAMOT OIL; CITRUS MAXIMA FRUIT RIND OIL; COCONUT OIL; GLYCERIN; GLYCERYL MONOSTEARATE; HEPTYL UNDECYLENATE; LAVENDER OIL; METHYLENE BLUE; RICE BRAN OIL; PEG-100 STEARATE; GERANIUM OIL, ALGERIAN TYPE; PHENOXYETHANOL; POLYSORBATE 60; SORBITAN MONOLAURATE; .ALPHA.-TOCOPHEROL ACETATE; WATER; XANTHAN GUM

Bluevado Sunfix Sunscreen

Active Ingredients

Zinc Oxide 8.2%
Titanium Dioxide 2.8%

Purpose

Sunscreen

Uses

- Helps prevent sunburn
- If used with other sun protection measures (see Directions) decreases the risk of skin cancer and early skin aging.

Warnings:

- For external use only
- Do not useon damaged or broken skin.
- When using thus productkeep out of eyes.
  Rinse with water to remove.
- Stop use and ask a physicianif rash occurs.

Keep out of reach of children.

If product is swallowed, get medical help or contact a Poison Control Center right away.

Directions:

- Apply liberally 15 minutes before sun exposure
- Reapply: after 40 minutes of swimming or sweating; immediately after towel drying; at least every 2 hours
- Sun Protection Measures.Spending time in the sun increases your risk of skin cancer and early skin aging. To decrease this risk, regularly use a sunscreen with a broad spectrum SPF of 15 or higher and other sun protection measures including:
  - Limit time in the sun, especially from 10 a.m. – 2 p.m.
  - Wear long sleeves shirts, pants, hats, and sunglasses
  - Children under 6 months: Ask a physician.

Other Information:

Protect this product from excessive heat and direct sun. Provides moderate protection against sunburn.

Inactive Ingredients:

Argania Spinosa (Argan) Kernel Oil, Ascorbyl Palmitate, Bisabolol Butyrospermum Parkii (Shea) Butter, C13-15 Alkane, Caprylic/Capric Triglyceride, Capryloyl Glycerin/Sebacic Acid Copolymer, Cetearyl Alcohol, Cetyl Alcohol, Citrus Aurantium Bergamia (Bergamot) Peel Oil, Citrus Grandis (Grapefruit) Peel Oil, Cocos Nucifera (Coconut) Oil, Glycerin, Glyceryl Stearate, Heptyl Undecylenate, Jojoba Esters, Lavandula Angustifolia (Lavender) Oil, Methylene Blue, Oryza Sativa (Rice) Bran Oil, PEG-100 Stearate, Pelargonium Graveolens (Geranium) Leaf Oil, Phenoxyethanol, Polyhydroxystearic Acid, Polysorbate 60, Sorbitan Laurate, Tocopheryl Acetate, Water (Aqua), Xanthan Gum.

Package/Label Principal Display Panel

Bluelene®

Bluevado™
SunFix
Protects, Repairs & Moisturizes
SPF 21

SPF DAY CREAM

Revolutionary Anti-aging Technology
Mineral + Methylene Blue
Broad-Spectrum UVA/UVB Coverage

CORAL SAFE

3 fl oz (90 mL)

Manufactured for Mblue Labs,
Bethesda, MD 20817, USA
1-800-988-8068
www.bluelene.com

Label